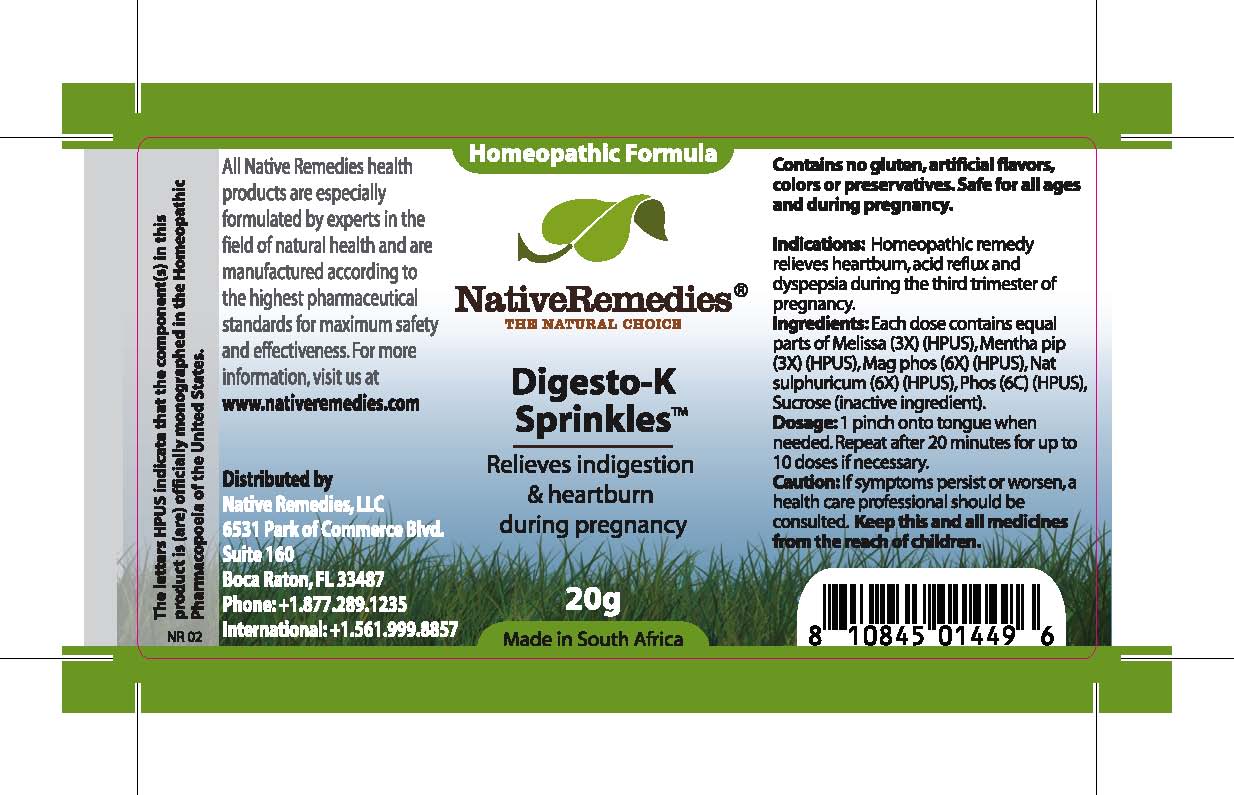 DRUG LABEL: Digesto-K
NDC: 68647-198 | Form: GRANULE
Manufacturer: Feelgood Health
Category: homeopathic | Type: HUMAN OTC DRUG LABEL
Date: 20100818

ACTIVE INGREDIENTS: LEMON BALM OIL 3 [hp_X]/40 mg; PEPPERMINT 3 [hp_X]/40 mg; MAGNESIUM PHOSPHATE, DIBASIC TRIHYDRATE 6 [hp_X]/40 mg; SODIUM SULFATE 6 [hp_X]/40 mg; PHOSPHORUS 6 [hp_C]/40 mg
INACTIVE INGREDIENTS: SUCROSE

DIGESTO-K

PURPOSE

Relieves indigestion and heartburn during pregnancy

INDICATIONS AND USAGE

Indications: Homeopathic remedy relieves heartburn, acid reflux and dyspepsia during the third trimester of pregnancy.

DOSAGE AND ADMINISTRATION

Dosage: 1 pinch onto tongue when needed. Repeat after 20 minutes for up to 10 doses if necessary.

GENERAL PRECAUTIONS

Caution: If symptoms persist or worsen, a health care professional should be consulted. Keep this and all medicines from the reach of children.

ACTIVE INGREDIENT

Ingredients: Each dose contains equal parts of Melissa (3X) (HPUS), Mentha pip (3X) (HPUS), Mag phos (6X) (HPUS), Nat sulphuricum (6X) (HPUS), Phos (6C) (HPUS)

Sucrose (inactive ingredient).

PREGNANCY

If symptoms persist or worsen, a health care professional should be consulted.

WARNINGS

Contains no gluten, artificial flavors, colors or preservatives. Safe for all ages and during pregnancy.

PATIENT COUNSELING INFORMATION

All Native Remedies health products are especially formulated by experts in the field of natural health and are manufactured according to the highest pharmaceutical standards for maximum safety and effectiveness. For more information, visit us at www.nativeremedies.com

Distributed by

Native Remedies, LLC

6531 Park of Commerce Blvd.

Suite 160

Boca Raton, FL 33487

Phone: 1.877.289.1235

International: + 1.561.999.8857

The letters HPUS indicate that the component(s) in this product is (are) officially monographed in the Homeopathic Pharmacopoeia of the United States.

KEEP OUT OF REACH OF CHILDREN

Keep this and all medicines from the reach of children.